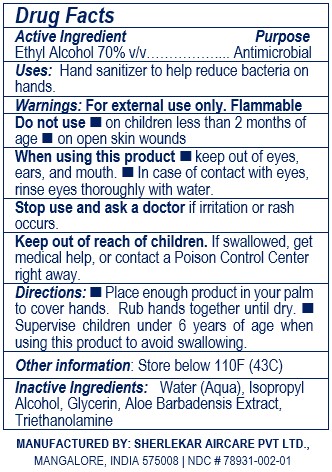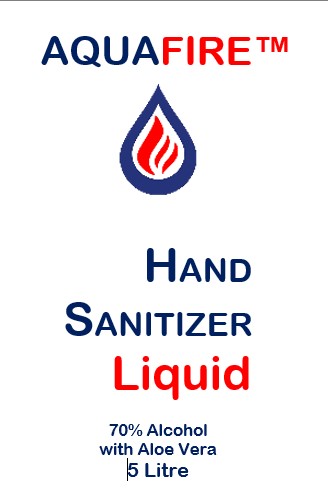 DRUG LABEL: AQUAFIRE
NDC: 78931-002 | Form: LIQUID
Manufacturer: SHERLEKAR AIRCARE PRIVATE LIMITED
Category: otc | Type: HUMAN OTC DRUG LABEL
Date: 20200717

ACTIVE INGREDIENTS: ALCOHOL 70 mL/100 mL
INACTIVE INGREDIENTS: GLYCERIN; WATER; ALOE VERA LEAF; ISOPROPYL ALCOHOL; TROLAMINE

Liquid

This is a hand sanitizer manufactured according to the Temporary Policy for Preparation of Certain Alcohol-Based Hand Sanitizer Products During the Public Health Emergency (CoViD-19); Guidance for Industry.

Active Ingredient(s)

Alcohol 70% v/v. Purpose: Antimicrobial

Purpose

Antimicrobial, Hand Sanitizer

Use

Hand sanitizer to help reduce bacteria on hands.

Warnings

For external use only. Flammable. Keep away from heat or flame

Do not use

- on children less than 2 months of age
- on open skin wounds

When using this product keep out of eyes, ears, and mouth. In case of contact with eyes, rinse eyes thoroughly with water.
Stop use and ask a doctor if irritation or rash occurs. These may be signs of a serious condition.
Keep out of reach of children. If swallowed, get medical help or contact a Poison Control Center right away.

Stop use and ask a doctor if irritation or rash occurs. These may be signs of a serious condition.

Keep out of reach of children. If swallowed, get medical help or contact a Poison Control Center right away.

Directions

- Place enough product on hands to cover all surfaces. Rub hands together until dry.
- Supervise children under 6 years of age when using this product to avoid swallowing.

Other information

- Store below 110F (43C)

Inactive ingredients

Water (Aqua), Isopropyl Alcohol, Glycerin, Aloe Barbadensis Extract, Triethanolamine

Package Label - Principal Display Panel

5 L NDC: 78931-002-01